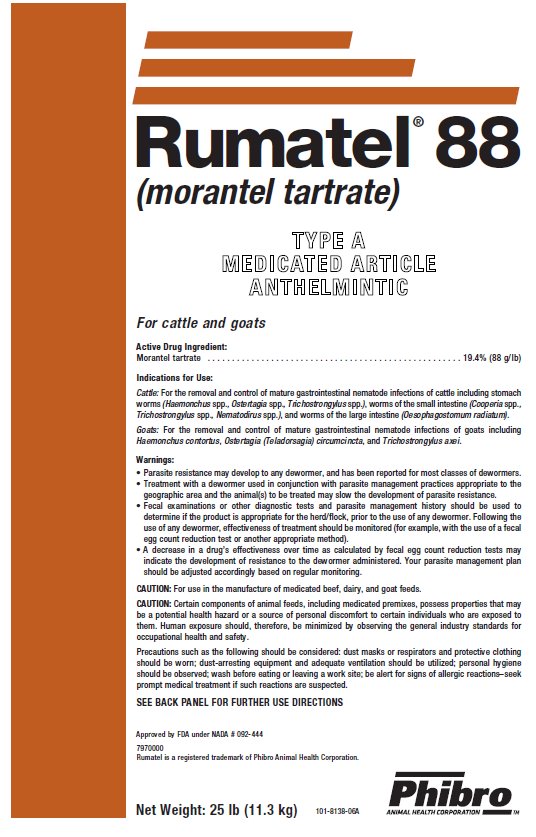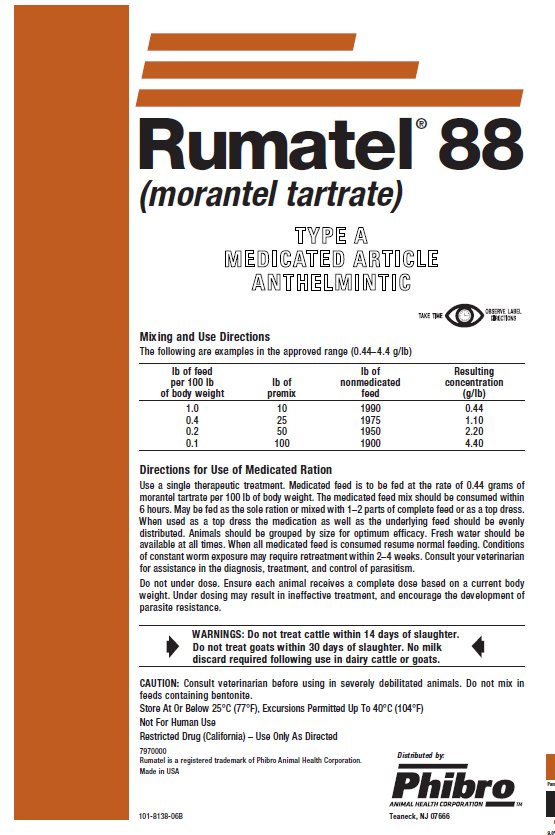 DRUG LABEL: Rumatel 88
NDC: 66104-2400 | Form: POWDER
Manufacturer: Phibro Animal Health
Category: animal | Type: OTC TYPE A MEDICATED ARTICLE ANIMAL DRUG LABEL
Date: 20190627

ACTIVE INGREDIENTS: MORANTEL TARTRATE 88 g/0.45 kg
INACTIVE INGREDIENTS: MINERAL OIL; SODIUM ALUMINOSILICATE; CALCIUM CARBONATE; SOYBEAN

Rumatel® 88
(morantel tartrate)
TYPE A MEDICATED ARTICLE

For cattle and goats

Active Drug Ingredient:

Morantel tartrate . . . . . . . . . . . . . . . . . . . . . . . . . . . . . . . . . . . . . . . . . . . 19.4% (88 g/lb)

Indications for Use:

Cattle: For the removal and control of mature gastrointestinal nematode infections of cattle including stomach worms (Haemonchus spp., Ostertagia spp., Trichostrongylus spp.), worms of the small intestine (Cooperia spp., Trichostrongylus spp., Nematodirus spp.), and worms of the large intestine (Oesophagostomum radiatum).

Goats: For the removal and control of mature gastrointestinal nematode infections of goats including Haemonchus contortus, Ostertagia (Teladorsagia) circumcincta, and Trichostrongylusaxei.

Warnings: Parasite resistance may develop to any dewormer, and has been reported for most classes of dewormers. Treatment with a dewormer used in conjunction with parasite management practices appropriate to the geographic area and the animal(s) to be treated may slow the development of parasite resistance. Fecal examinations or other diagnostic tests and parasite management history should be used to determine if the product is appropriate for the herd/flock, prior to the use of any dewormer. Following the use of any dewormer, effectiveness of treatment should be monitored (for example, with the use of fecal egg count reduction test or another appropriate method). A decrease in a drug’s effectiveness over time as calculated by fecal egg count reduction tests may indicate the development of resistance to the dewormer administered. Your parasite management plan should be adjusted accordingly based on regular monitoring. CAUTION:

For use in the manufacture of medicated beef, dairy, and goat feeds.

CAUTION: Certain components of animal feeds, including medicated premixes, possess properties that may be a potential health hazard or a source of personal discomfort to certain individuals who are exposed to them. Human exposure should, therefore, be minimized by observing the general industry standards for occupational health and safety.

Precautions such as the following should be considered: dust masks or respirators and protective clothing should be worn; dust-arresting equipment and adequate ventilation should be utilized; personal hygiene should be observed; wash before eating or leaving a work site; be alert for signs of allergic reactions–seek prompt medical treatment if such reactions are suspected.

Mixing and Use Directions

The following are examples in the approved range (0.44–4.4 g/lb)

lb of feed per 100 lb of body weight | lb of premix | lb of nonmedicated feed | Resulting concentration (g/lb)
1.0 | 10 | 1990 | 0.44
0.4 | 25 | 1975 | 1.10
0.2 | 50 | 1950 | 2.20
0.1 | 100 | 1900 | 4.40

Directions for Use of Medicated Ration

Use a single therapeutic treatment. Medicated feed is to be fed at the rate of 0.44 grams of morantel tartrate per 100 lb of body weight. The medicated feed mix should be consumed within 6 hours. May be fed as the sole ration or mixed with 1–2 parts of complete feed or as a top dress. When used as a top dress the medication as well as the underlying feed should be evenly distributed. Animals should be grouped by size for optimum efficacy. Fresh water should be available at all times. When all medicated feed is consumed resume normal feeding. Conditions of constant worm exposure may require retreatment within 2–4 weeks. Consult your veterinarian for assistance in the diagnosis, treatment, and control of parasitism.

Do not under dose. Ensure each animal receives a complete dose based on a current body weight. Under dosing may result in ineffective treatment, and encourage the development of parasite resistance.

WARNINGS:

Do not treat cattle within 14 days of slaughter.

Do not treat goats within 30 days of slaughter. No milk

discard required following use in dairy cattle or goats.

CAUTION: Consult veterinarian before using in severely debilitated animals. Do not mix in feeds containing bentonite.

Restricted Drug (California) – USE AS DIRECTED

Store At or Below 25°C(77°F), Excursions Permitted Up to 40°C (104°F)

Not For Human Use

SEE BACK PANEL FOR FURTHER USE DIRECTIONS

Net Weight: 25 lb (11.3 kg)

Approved by FDA under NADA #092-444

7970000

101-8318-06B

Made in USA